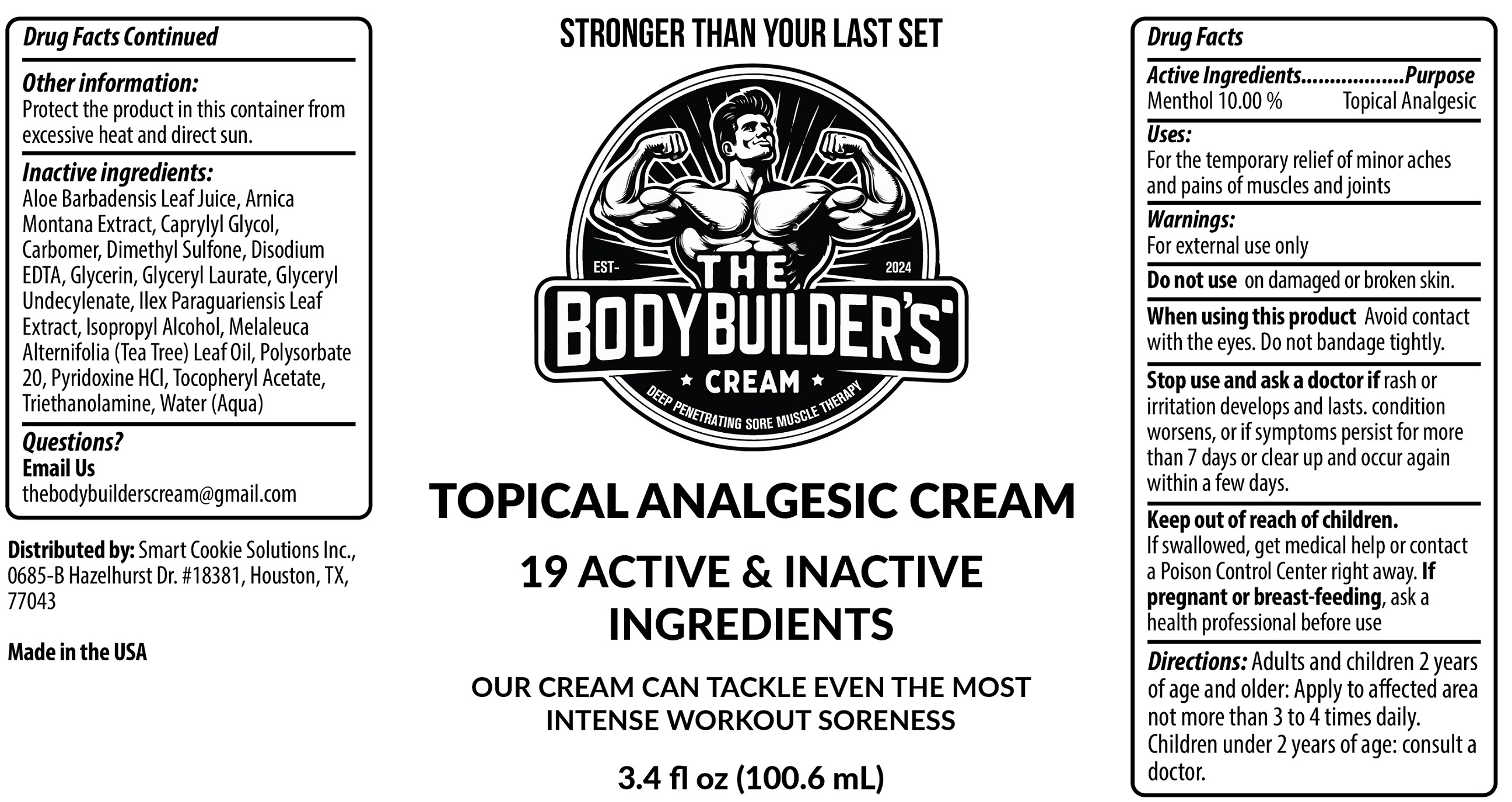 DRUG LABEL: The Body Builders Cream
NDC: 87282-912 | Form: CREAM
Manufacturer: Smart Cookie Solutions
Category: otc | Type: HUMAN OTC DRUG LABEL
Date: 20251222

ACTIVE INGREDIENTS: MENTHOL 100 mg/1 mL
INACTIVE INGREDIENTS: ALOE VERA LEAF JUICE; ARNICA MONTANA WHOLE; CAPRYLYL GLYCOL; CARBOMER HOMOPOLYMER, UNSPECIFIED TYPE; DIMETHYL SULFONE; EDETATE DISODIUM; GLYCERIN; GLYCERYL LAURATE; ILEX PARAGUARIENSIS LEAF; ISOPROPYL ALCOHOL; TEA TREE OIL; POLYSORBATE 20; PYRIDOXINE HYDROCHLORIDE; .ALPHA.-TOCOPHEROL ACETATE; TROLAMINE; WATER

The Body Builder's Cream

Active Ingredients

Menthol 10.00%

Purpose

Topical Analgesic

Uses:

For the temporary relief of minor aches and pains of muscles and joints

Warnings:

For external use only

Do not use

on damaged or broken skin.

When using this product

Avoid contact with the eyes. Do not bandage tightly.

Stop use and ask a doctor if

rash or irritation develops and lasts. condition worsens, or if symptoms persist for more than 7 days or clear up and occur again within a few days.

Keep out of reach of children.

If swallowed, get medical help or contact a Poison Control Center right away.

If pregnant or breast-feeding,

ask a health professional before use

Directions:

Adults and children 2 years of age and older: Apply to affected area not more than 3 to 4 times daily.
Children under 2 years of age: consult a doctor.

Other information:

Protect the product in this container from excessive heat and direct sun.

Inactive ingredients:

Aloe Barbadensis Leaf Juice, Arnica Montana Extract, Caprylyl Glycol, Carbomer, Dimethyl Sulfone, Disodium EDTA, Glycerin, Glyceryl Laurate, Glyceryl Undecylenate, Ilex Paraguariensis Leaf Extract, Isopropyl Alcohol, Melaleuca Alternifolia (Tea Tree) Leaf Oil, Polysorbate 20, Pyridoxine HCl, Tocopheryl Acetate, Triethanolamine, Water (Aqua)

Questions?

Email Us
thebodybuilderscream@gmail.com